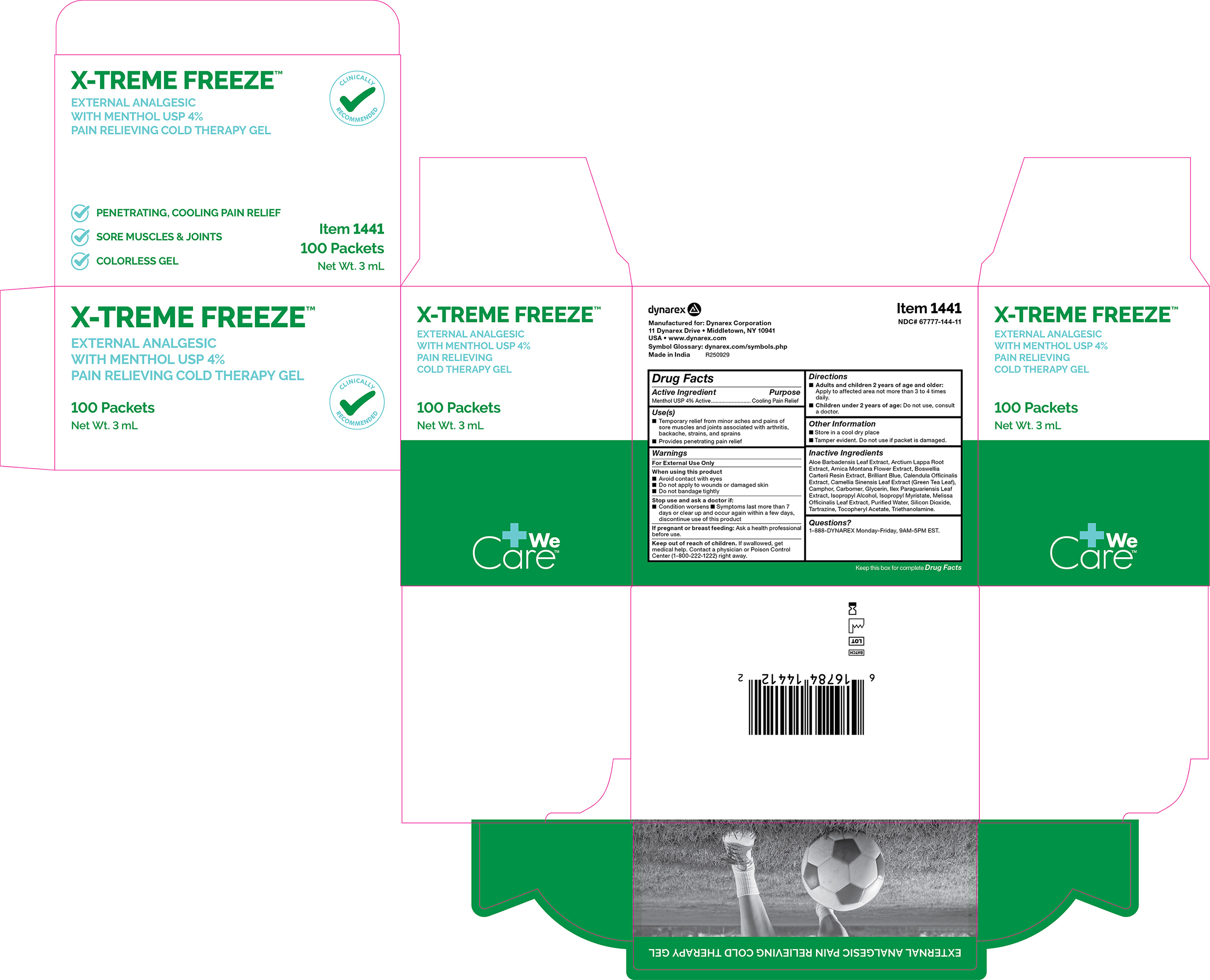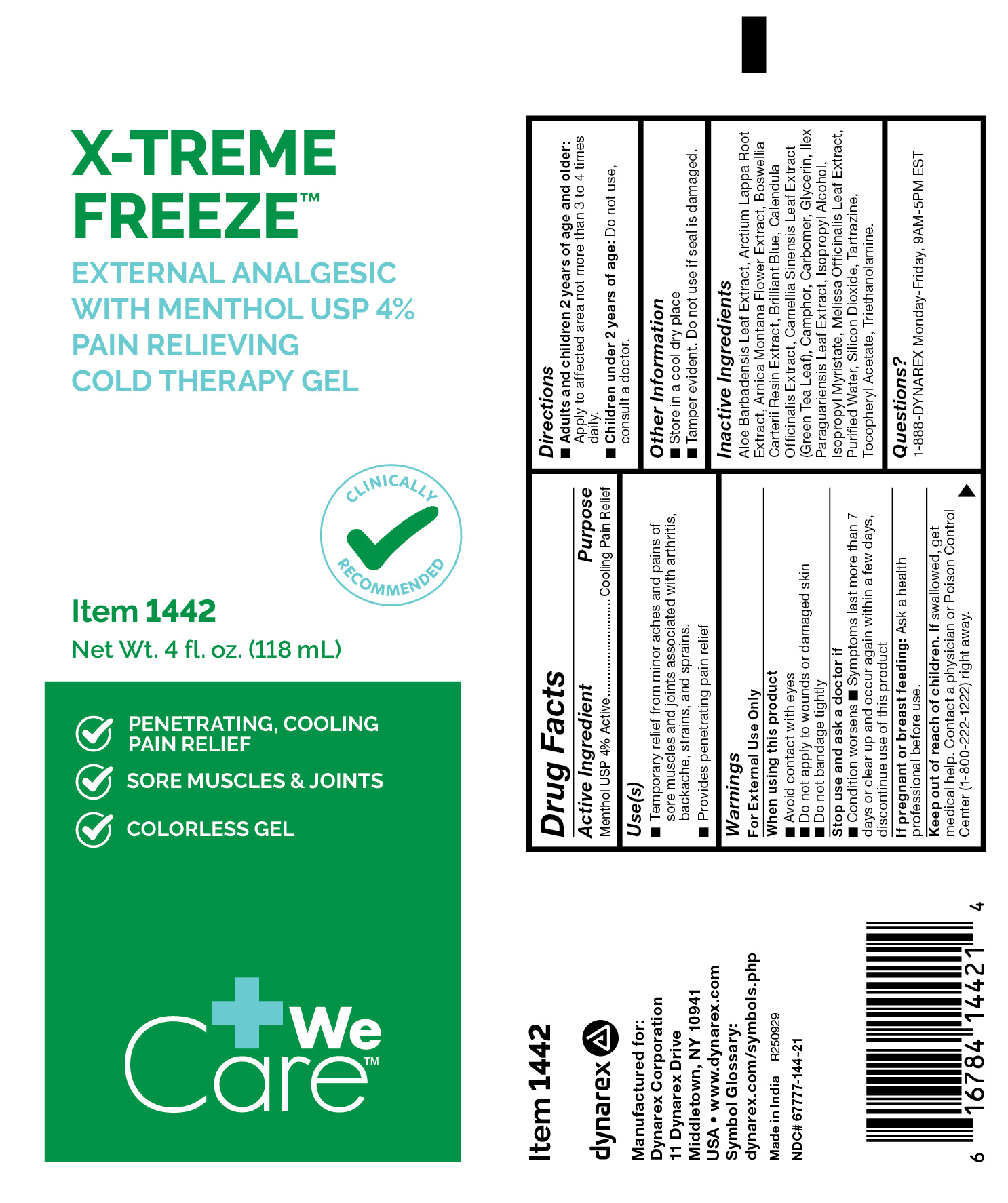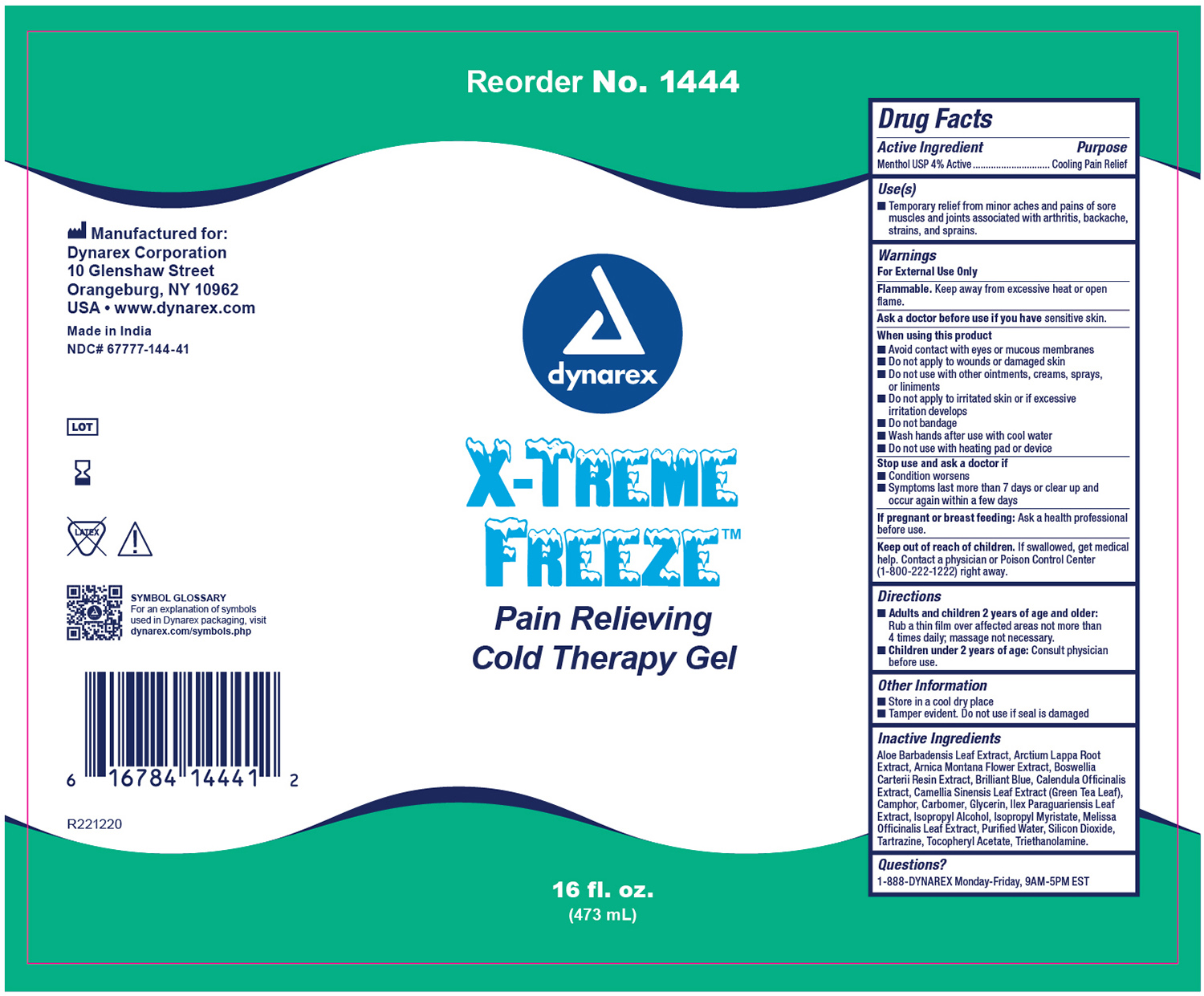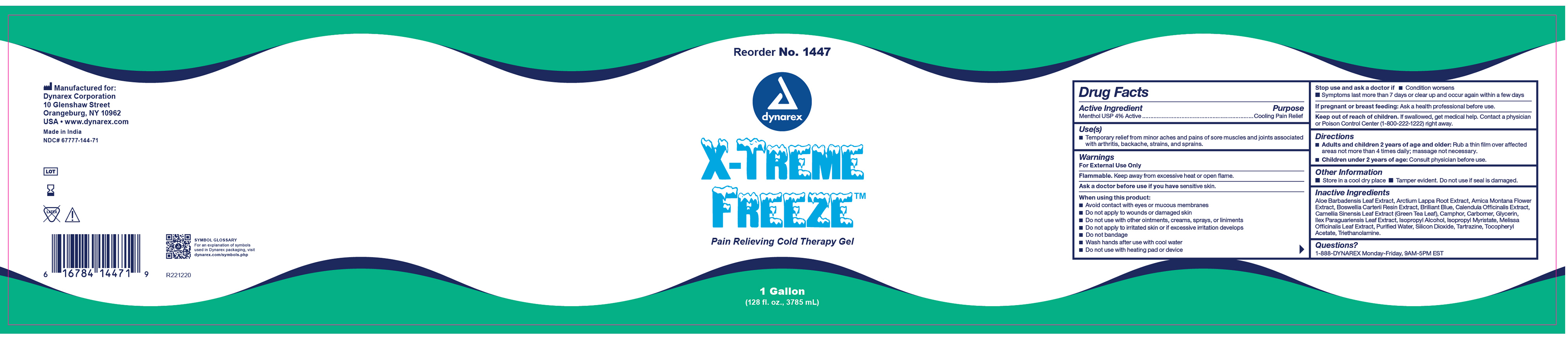 DRUG LABEL: X-Treme Freeze
NDC: 67777-144 | Form: GEL
Manufacturer: Dynarex Corporation
Category: otc | Type: HUMAN OTC DRUG LABEL
Date: 20260122

ACTIVE INGREDIENTS: MENTHOL 4 g/100 mL
INACTIVE INGREDIENTS: ISOPROPYL MYRISTATE; TROLAMINE; CARBOXYPOLYMETHYLENE; ALOE VERA LEAF; GLYCERIN; ISOPROPYL ALCOHOL; ARNICA MONTANA FLOWER; FRANKINCENSE; CALENDULA OFFICINALIS FLOWER; ILEX PARAGUARIENSIS LEAF; MELISSA OFFICINALIS LEAF; ARCTIUM LAPPA ROOT; GREEN TEA LEAF; ALPHA-TOCOPHEROL ACETATE; SILICON DIOXIDE; .ALPHA.,.ALPHA.-DIBROMO-D-CAMPHOR; FD&C YELLOW NO. 5; WATER; FD&C BLUE NO. 1

1441 Extreme Freeze NDC 67777-144-10
1442 Extreme Freeze NDC 67777-144-20
1444 Extreme Freeze NDC 67777-144-40
1447 Extreme Freeze NDC 67777-144-70

Active Ingredient

Menthol USP 4% Active

Purpose

Cooling Pain Relief

Use(s)

• Temporary relief from minor aches and pains of sore muscles and joints associated with arthritis, backache, strains, and sprains

• Provides penetrating pain relief

Warnings

For External Use Only

When using this product

• Avoid contact with eyes

• Do not apply to wounds or damaged skin

• Do not bandage tightly

Stop use and ask a doctor if:

• Condition worsens

• Symptoms last more than 7 days or clear up and occur again within a few days, discontinue use of this product

If pregnant or breast feeding:

Ask a health professional before use.

Keep out of reach of children

If swallowed, get medical help. Contact a physician or Poison Control Center (1-800-222-1222) right way.

Directions

- Adults and children 2 years of age or older: Apply to affected area not more than 3 to 4 times daily.
- Children under 2 years of age: Do not use, consult a doctor.

Other Information

• Store in a cool dry place

• Tamper evident. Do not use if seal is damaged.

Inactive Ingredients

Aloe Barbadensis Leaf Extract, Arctium Lappa Root Extract, Arnica Montana Flower Extract, Boswellia Certerii Resin Extract, Brilliant Blue, Calendula Officinalis Extract, Camellia Sinensis Leaf Extract (Green Tea Leaf), Camphor, Carbomer, Glycerin, Llex Paraguariensis Leaf Extract, Isopropyl Alcohol, Isopropyl Myristate, Melissa Officinalis Leaf Extract, Purified Water, Silicon Dioxide, Tartrazine, Tocopheryl Acetate, Triethanolamine

Questions?

1-888-DYNAREX Monday-Friday, 9AM-5PM EST